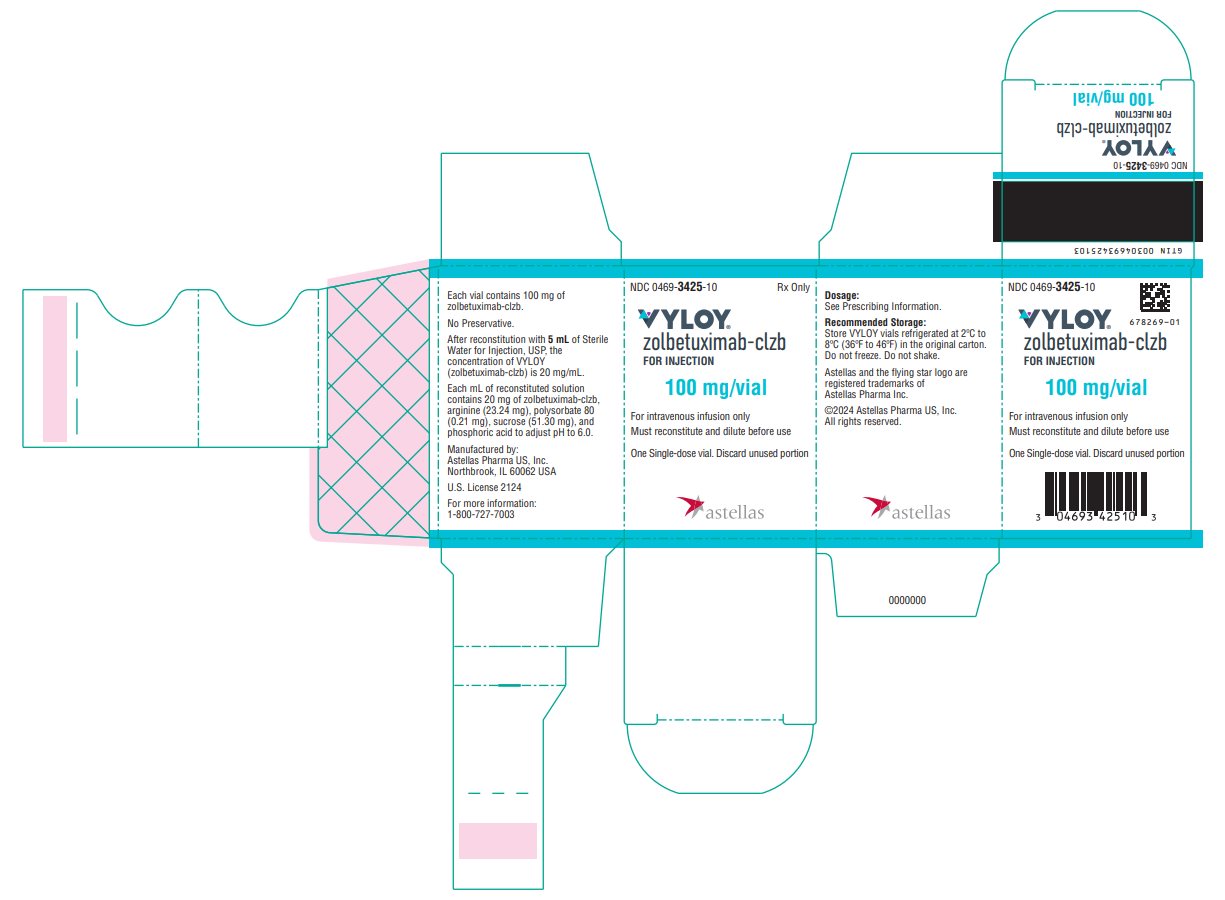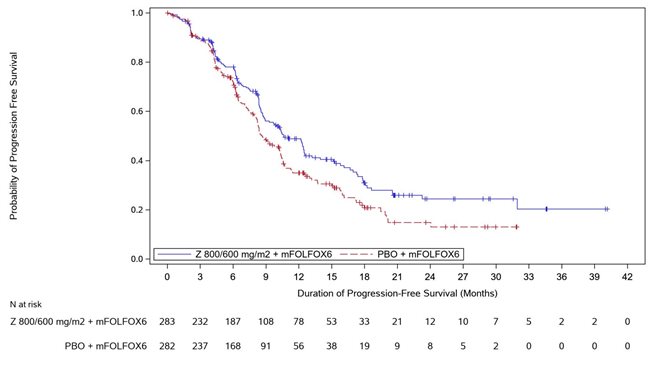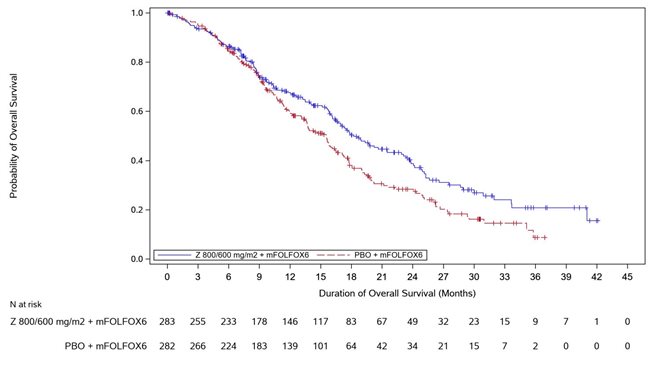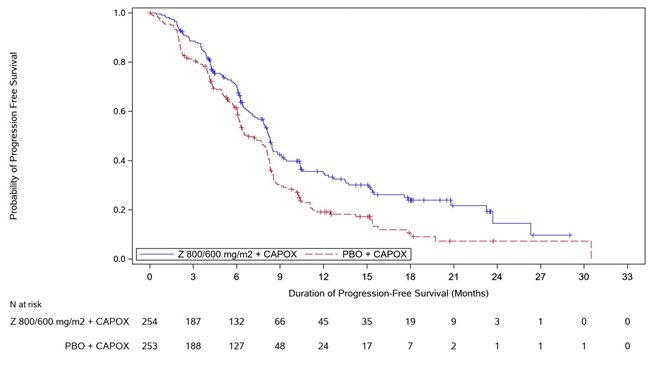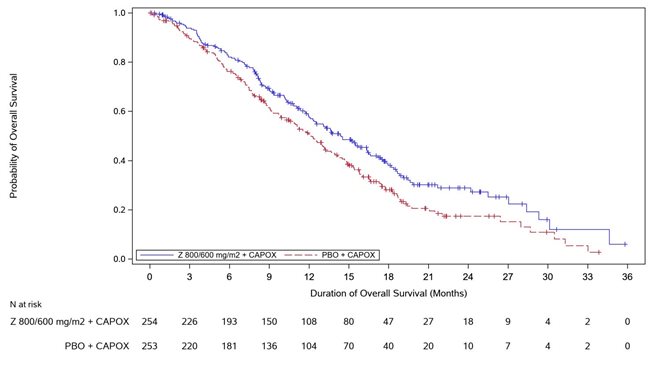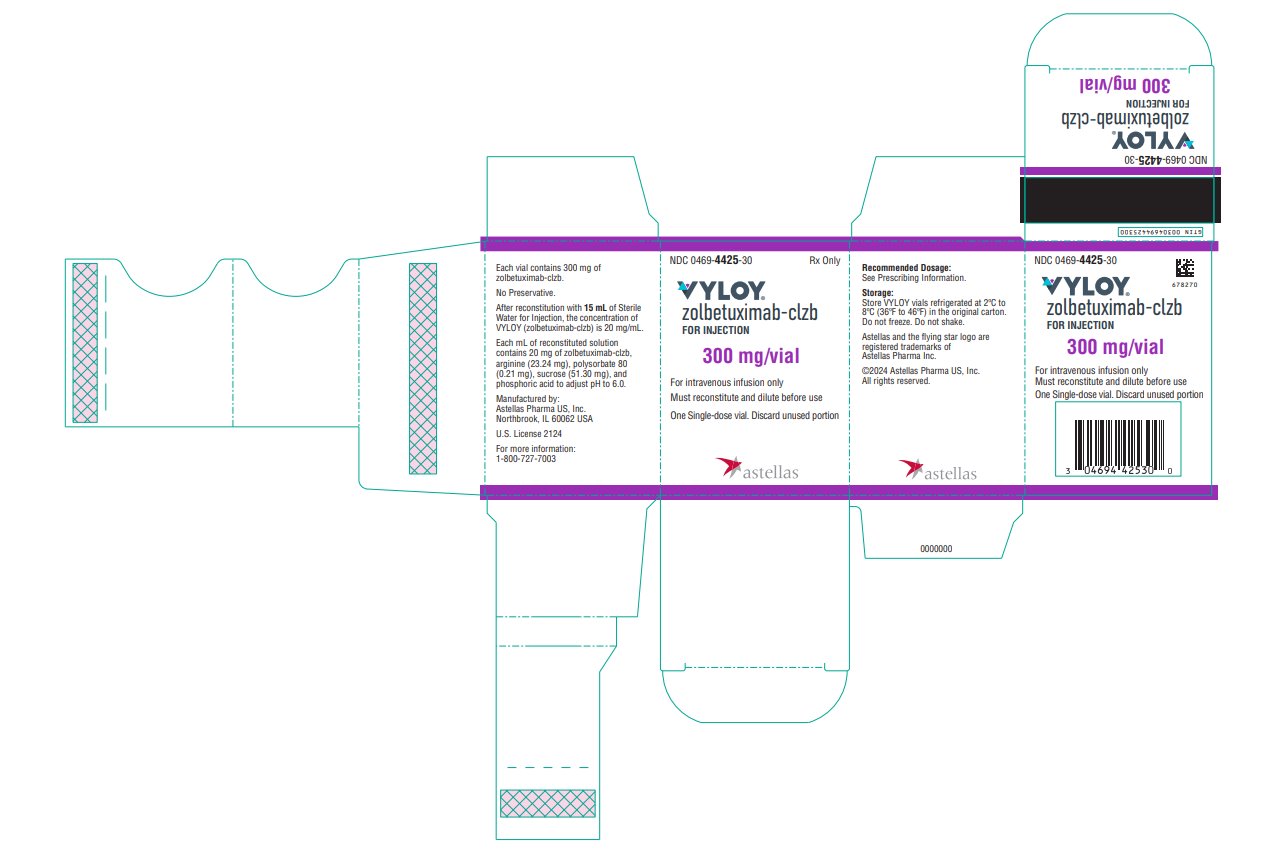 DRUG LABEL: VYLOY
NDC: 0469-3425 | Form: INJECTION, POWDER, FOR SUSPENSION
Manufacturer: Astellas Pharma US, Inc.
Category: prescription | Type: HUMAN PRESCRIPTION DRUG LABEL
Date: 20250612

ACTIVE INGREDIENTS: ZOLBETUXIMAB 20 mg/1 mL
INACTIVE INGREDIENTS: ARGININE 23.24 mg/1 mL; SUCROSE 51.30 mg/1 mL; POLYSORBATE 80 0.21 mg/1 mL; PHOSPHORIC ACID

HIGHLIGHTS OF PRESCRIBING INFORMATION

These highlights do not include all the information needed to use VYLOY safely and effectively. See full prescribing information for VYLOY.
VYLOY® (zolbetuximab-clzb) for injection, for intravenous use
Initial U.S. Approval: 2024

1 INDICATIONS AND USAGE

VYLOY is a claudin 18.2-directed cytolytic antibody and is indicated in combination with fluoropyrimidine- and platinum-containing chemotherapy for the first-line treatment of adults with locally advanced unresectable or metastatic human epidermal growth factor receptor 2 (HER2)-negative gastric or gastroesophageal junction adenocarcinoma whose tumors are claudin (CLDN) 18.2 positive as determined by an FDA-approved test (1).

2 DOSAGE AND ADMINISTRATION

- Administer by intravenous infusion only. Do not administer VYLOY as an intravenous push or bolus. (2.6)
- The recommended first dose of VYLOY is 800 mg/m^2 followed by 600 mg/m^2 every 3 weeks or 400 mg/m^2 every 2 weeks. (2.3)

3 DOSAGE FORMS AND STRENGTHS

For injection: 100 mg and 300 mg lyophilized powder in a single-dose vial. (3)

4 CONTRAINDICATIONS

None. (4)

5 WARNINGS AND PRECAUTIONS

- Hypersensitivity reactions including serious anaphylaxis reactions and serious and fatal infusion-related reactions have occurred. Monitor patients during and for at least 2 hours after infusion with VYLOY. Interrupt, slow the rate of infusion or permanently discontinue VYLOY based on severity and type of reaction. Premedicate with antihistamines for subsequent infusions after a hypersensitivity reaction. (2.4, 5.1)
- Severe nausea and vomiting: Premedicate patients with antiemetics prior to each infusion. Interrupt or permanently discontinue VYLOY based on the severity of the nausea and/or vomiting. Manage patients during and after infusion with antiemetics or fluid replacement. (2.4, 5.2)

6 ADVERSE REACTIONS

The most common adverse reactions (≥15%) for VYLOY in combination with mFOLFOX6 or CAPOX were nausea, vomiting, fatigue, decreased appetite, diarrhea, peripheral sensory neuropathy, abdominal pain, constipation, decreased weight, hypersensitivity reactions, and pyrexia.

The most common laboratory abnormalities (≥15%) for VYLOY in combination with mFOLFOX6 or CAPOX were decreased neutrophil count, decreased leucocyte count, decreased albumin, increased creatinine, decreased hemoglobin, increased glucose, decreased lymphocyte count, increased aspartate aminotransferase, decreased platelets, increased alkaline phosphatase, increased alanine aminotransferase, decreased glucose, decreased sodium, decreased phosphate, decreased potassium, and decreased magnesium (6.1).

To report SUSPECTED ADVERSE REACTIONS, contact Astellas Pharma US, Inc. at 1-800-727-7003 or FDA at 1-800-FDA-1088 or www.fda.gov/medwatch.

8 USE IN SPECIFIC POPULATIONS

Lactation: Advise not to breastfeed. (8.2)

FULL PRESCRIBING INFORMATION

1 INDICATIONS AND USAGE

VYLOY, in combination with fluoropyrimidine- and platinum-containing chemotherapy, is indicated for the first-line treatment of adults with locally advanced unresectable or metastatic human epidermal growth factor receptor 2 (HER2)‑negative gastric or gastroesophageal junction (GEJ) adenocarcinoma whose tumors are claudin (CLDN) 18.2 positive as determined by an FDA-approved test [see Dosage and Administration (2.1) and Clinical Studies (14)].

2 DOSAGE AND ADMINISTRATION

2.1 Patient Selection

Select adult patients with locally advanced unresectable or metastatic HER2-negative gastric or GEJ adenocarcinoma whose tumors are CLDN18.2 positive (defined as ≥75% of tumor cells demonstrating moderate to strong membranous CLDN18 immunohistochemical staining) for treatment with VYLOY in combination with fluoropyrimidine- and platinum-containing chemotherapy using an FDA-approved test [see Clinical Studies (14)].

Information on FDA-approved tests for the detection of CLDN18.2 is available at https://www.fda.gov/CompanionDiagnostics.

2.2 Prior to Administration

If a patient is experiencing nausea and/or vomiting prior to administration of VYLOY, the symptoms should be resolved to Grade ≤1 before administering the first infusion.

Premedication

Prior to each infusion of VYLOY, premedicate patients with a combination of antiemetics (e.g., NK-1 receptor blockers and/or 5-HT3 receptor blockers, as well as other drugs as indicated) for the prevention of nausea and vomiting [see Warnings and Precautions (5.2)].

2.3 Recommended Dosage

Administer VYLOY in combination with fluoropyrimidine- and platinum-containing chemotherapy as follows:

- First dose: 800 mg/m^2 intravenously.
- Subsequent doses:
  - 600 mg/m^2 intravenously every 3 weeks, or
  - 400 mg/m^2 intravenously every 2 weeks.
- Continue treatment until disease progression or unacceptable toxicity.

2.4 Dosage Modifications for Adverse Reactions

No dose reduction for VYLOY is recommended. Adverse reactions for VYLOY are managed by reducing the infusion rate, interruption of the infusion, withholding the dose, and/or permanently discontinuing VYLOY as described in Table 1.

Table 1. Recommended Dose Modifications for VYLOY for Adverse Reactions
Adverse Reaction | Severity [Toxicity was graded per National Cancer Institute Common Terminology Criteria for Adverse Events Version 5.0 (NCI-CTCAE v5.0).] | Dose Modification
Hypersensitivity or Infusion-related reactions [see Warnings and Precautions (5.1)]. | Grade 2 | - Interrupt the infusion until Grade ≤1, then resume at a reduced infusion rate for the remaining infusion. - Premedicate and administer the next infusion per the infusion rates in Table 2.
Hypersensitivity or Infusion-related reactions [see Warnings and Precautions (5.1)]. | Grade 3 [Follow Grade 2 management for Grade 3 infusion-related nausea and vomiting.] or 4 or anaphylaxis | - Immediately stop the infusion and permanently discontinue.

2.5 Preparation

Reconstitution

- Calculate the recommended dose based on the patient’s body surface area as described in Section 2.3 to determine the total volume and number of vials needed.
- Reconstitute each vial of VYLOY to achieve a concentration of 20 mg/mL as follows:
  - 100 mg vial add 5 mL of Sterile Water for Injection.
  - 300 mg vial add 15 mL of Sterile Water for Injection.
- Slowly add the Sterile Water for Injection into the VYLOY vial, and direct the stream toward the inside wall of the vial. Do not inject directly onto the lyophilized powder.
- Slowly swirl each vial until the contents are completely dissolved. Allow the reconstituted vial(s) to settle until the bubbles are gone. Do not shake the vial.
- Visually inspect the reconstituted solution for particulate matter and discoloration. The reconstituted solution should be clear to slightly opalescent, colorless to slight yellow and free of visible particles. Discard any vial with visible particles or discoloration.
- Store reconstituted vial(s) at room temperature 15°C to 30°C (59°F to 86°F) for up to 5 hours if not used immediately. This product does not contain a preservative.

Dilution

- Withdraw the required volume of reconstituted VYLOY vial(s) and transfer into an infusion bag containing 0.9% Sodium Chloride Injection, to a final concentration of 5 mg/mL.
  - The diluted solution of VYLOY is compatible with intravenous infusion bags composed of polyethylene (PE), polypropylene (PP), polyvinyl chloride (PVC) [with either Di(2-ethylhexyl) phthalate (DEHP) or, Trioctyl trimellitate (TOTM) plasticizers], ethylene propylene copolymer, ethylene-vinyl acetate (EVA) copolymer, PP and styrene-ethylene-butylene-styrene copolymer.
  - The diluted solution of VYLOY is compatible with infusion tubing composed of PE, PVC [with DEHP, TOTM or Di(2-ethylhexyl) terephthalate plasticizers], polybutadiene (PB), or elastomer modified polypropylene with in-line filter membranes composed of polyethersulfone (PES) or polysulfone.
- Mix diluted solution by gentle inversion. Do not shake the bag.
- Visually inspect the infusion bag for any particulate matter prior to use. The diluted solution should be free of visible particles. Do not use the infusion bag if particulate matter is observed.
- Discard any unused portion left in the single-dose vials.

Storage of diluted infusion

- Store the prepared infusion bag:
  - At room temperature 15°C to 30°C (59°F to 86°F) for no longer than 6 hours from the end of the preparation of the infusion bag to the completion of the infusion.
  - Under refrigeration at 2°C to 8°C (36°F to 46°F) for no longer than 16 hours from the end of the preparation of the infusion bag to the completion of the infusion. Do not freeze.

2.6 Administration

- Administer VYLOY as an intravenous infusion only. Do NOT administer as an intravenous push or bolus.
- If VYLOY and fluoropyrimidine- and platinum-containing chemotherapy are administered on the same day, VYLOY must be administered first.
- No incompatibilities have been observed with
  - closed system transfer devices composed of PP, PE, stainless steel, silicone (rubber/oil/resin), polyisoprene, PVC with TOTM plasticizer, acrylonitrile-butadiene-styrene (ABS) copolymer, methyl methacrylate-ABS copolymer, thermoplastic elastomer, polytetrafluoroethylene, polycarbonate, PES, acrylic copolymer, polybutylene terephthalate, PB, or EVA copolymer.
  - central ports composed of silicone rubber, titanium alloy or PVC with TOTM plasticizer.
- In-line filters (pore size of 0.2 μm composed of materials listed above) are recommended to be used during administration.
- Do NOT co-administer other drugs through the same infusion line.
- Immediately administer the infusion as described in Table 2. To minimize the risk of adverse reactions, begin each infusion at a slower rate for 30 to 60 minutes; if tolerated, gradually increase the rate as described in Table 2.
- If the infusion time exceeds the recommended storage time (6 hours from end of preparation of infusion solution at room temperature or 16 hours from end of preparation of infusion solution under refrigeration), the infusion bag must be discarded and a new infusion bag prepared to continue the infusion.

Infusion Rate Recommendations

Table 2. Infusion Rates Recommended for Each VYLOY Infusion
VYLOY Dose |  | Initial Infusion Rate; (first 30-60 minutes) [In the absence of adverse reactions after 30 to 60 minutes, the infusion rate can be increased to the subsequent infusion rate as tolerated.] | Subsequent Infusion Rate
First Dose | 800 mg/m^2 | 100 mg/m^2/hr | 200-265 mg/m^2/hr
Subsequent Doses | 600 mg/m^2 every 3 weeks | 75 mg/m^2/hr | 150-265 mg/m^2/hr
Subsequent Doses | or | or | or
Subsequent Doses | 400 mg/m^2 every 2 weeks | 50 mg/m^2/hr | 100-200 mg/m^2/hr

3 DOSAGE FORMS AND STRENGTHS

For injection: 100 mg and 300 mg of zolbetuximab-clzb as a white to off-white lyophilized powder in a single-dose vial.

4 CONTRAINDICATIONS

None.

5 WARNINGS AND PRECAUTIONS

5.1 Hypersensitivity reactions, including anaphylaxis reactions, and infusion related reactions

Hypersensitivity reactions, including serious anaphylaxis reactions, and serious and fatal infusion-related reactions (IRR) have been reported in clinical studies when VYLOY has been administered.

Any grade hypersensitivity reactions, including anaphylactic reactions, occurring with VYLOY in combination with mFOLFOX6 or CAPOX was 18%. Severe (Grade 3 or 4) hypersensitivity reactions, including anaphylactic reactions, occurred in 2% of patients. Seven patients (1.3%) permanently discontinued VYLOY for hypersensitivity reactions, including two patients (0.4%) who permanently discontinued VYLOY due to anaphylactic reactions. Seventeen (3.2%) patients required dose interruption, and three patients (0.6%) required infusion rate reduction due to hypersensitivity reactions.

All grade IRRs occurred in 3.2% in patients administered VYLOY in combination with mFOLFOX6 or CAPOX. Severe (Grade 3) IRRs occurred in 2 (0.4%) patients who received VYLOY. An IRR led to permanent discontinuation of VYLOY in 2 (0.4%) patients and dose interruption in 7 (1.3%) patients. The infusion rate was reduced for VYLOY for 2 (0.4%) patients due to an IRR.

Monitor patients during infusion with VYLOY and for 2 hours after completion of infusion or longer if clinically indicated, for hypersensitivity reactions with symptoms and signs that are highly suggestive of anaphylaxis (urticaria, repetitive cough, wheeze and throat tightness/change in voice). Monitor patients for signs and symptoms of IRRs including nausea, vomiting, abdominal pain, salivary hypersecretion, pyrexia, chest discomfort, chills, back pain, cough and hypertension.

If a severe or life-threatening hypersensitivity or IRR reaction occurs, discontinue VYLOY permanently, treat symptoms according to standard medical care, and monitor until symptoms resolve. For any Grade 2 hypersensitivity or IRR, interrupt the VYLOY infusion until Grade ≤1, then resume at a reduced infusion rate for the remaining infusion. Premedicate the patient with antihistamines for the subsequent infusions, administer per the infusion rates in Table 2 and closely monitor the patient for symptoms and signs of a hypersensitivity reaction. The infusion rate may be gradually increased as tolerated [see Dosage and Administration (2.4)].

5.2 Severe Nausea and Vomiting

VYLOY is emetogenic. Nausea and vomiting occurred more often during the first cycle of treatment.

All grade nausea and vomiting occurred in 82% and 67%, respectively, of patients treated with VYLOY in combination with mFOLFOX6 and 69% and 66% in combination with CAPOX, respectively. Severe (Grade 3) nausea occurred in 16% and 9% of patients treated with VYLOY in combination with mFOLFOX6 or CAPOX respectively. Severe (Grade 3) vomiting occurred in 16% and 12% of patients treated with VYLOY in combination with mFOLFOX6 or CAPOX.

Nausea led to permanent discontinuation of VYLOY in combination with mFOLFOX6 or CAPOX in 18 (3.4%) patients and dose interruption in 147 (28%) patients. Vomiting led to permanent discontinuation of VYLOY in combination with mFOLFOX6 or CAPOX in 20 (3.8%) patients and dose interruption in 150 (28%) patients.

Pretreat with antiemetics prior to each infusion of VYLOY [see Dosage and Administration (2.2)]. Manage patients during and after infusion with antiemetics or fluid replacement.

Interrupt the infusion, or permanently discontinue VYLOY based on severity [see Dosage and Administration (2.4)].

6 ADVERSE REACTIONS

The following serious adverse reactions are described elsewhere in the labeling:

- Hypersensitivity Reactions, including anaphylaxis, and infusion related reactions [see Warnings and Precautions (5.1)].
- Severe Nausea and Vomiting [see Warnings and Precautions (5.2)].

6.1 Clinical Trials Experience

Because clinical trials are conducted under widely varying conditions, adverse reaction rates observed in the clinical trials of a drug cannot be directly compared to rates in the clinical trials of another drug and may not reflect the rates observed in practice.

The pooled safety population described in the WARNINGS AND PRECAUTIONS reflect exposure to VYLOY in 533 patients at an 800 mg/m^2 initial dose followed by subsequent doses of 600 mg/m^2 every 3 weeks in combination with fluoropyrimidine- and platinum-containing chemotherapy in the SPOTLIGHT (279) and GLOW (254) studies. Among 533 patients who received VYLOY in these studies, 47% were exposed for ≥6 months and 20% were exposed for ≥12 months.

In this pooled population, the most common (≥15%) adverse reactions, were nausea, vomiting, fatigue, decreased appetite, diarrhea, peripheral sensory neuropathy, abdominal pain, constipation, decreased weight, hypersensitivity reactions, and pyrexia. The most common (≥15%) laboratory abnormalities in the pooled population were decreased neutrophil count, decreased leucocyte count, decreased albumin, increased creatinine, decreased hemoglobin, increased glucose, decreased lymphocyte count, increased aspartate aminotransferase, decreased platelets, increased alkaline phosphatase, increased alanine aminotransferase, decreased glucose, decreased sodium, decreased phosphate, decreased potassium, and decreased magnesium.

SPOTLIGHT

The safety of VYLOY was evaluated in SPOTLIGHT in patients with locally advanced unresectable or metastatic gastric or GEJ cancer who received at least one dose of VYLOY at an 800 mg/m^2 initial dose followed by 600 mg/m^2 subsequent doses every 3 weeks in combination with mFOLFOX6 [see Clinical Studies (14)]. The median duration of exposure to VYLOY in combination with mFOLFOX6 was 6.2 months (range: 1 day to 40.9 months).

Serious adverse reactions occurred in 45% of patients treated with VYLOY in combination with mFOLFOX6; the most common serious adverse reactions (≥2%) were vomiting (8%), nausea (7%), neutropenia (2.9%), febrile neutropenia (2.9%), diarrhea (2.9%), intestinal obstruction (3.2%), pyrexia (2.5%), pneumonia (2.5%), respiratory failure (2.2%), pulmonary embolism (2.2%), decreased appetite (2.1%) and sepsis (2.0%). Fatal adverse reactions occurred in 5% of patients who received VYLOY in combination with mFOLFOX6 including sepsis (1.4%), pneumonia (1.1%), respiratory failure (1.1%), intestinal obstruction (0.7%), acute hepatic failure (0.4%), acute myocardial infarction (0.4%), death (0.4%), disseminated intravascular coagulation (0.4%), encephalopathy (0.4%), and upper gastrointestinal hemorrhage (0.4%).

Permanent discontinuation of VYLOY due to an adverse reaction occurred in 20% of patients; the most common adverse reactions leading to discontinuation (≥2%) were nausea and vomiting.

Dosage interruptions of VYLOY due to an adverse reaction occurred in 75% of patients; the most common adverse reactions leading to dose interruption (≥5%) were nausea, vomiting, neutropenia, abdominal pain, fatigue, and hypertension.

Tables 3 and 4 summarize the most common (≥15%) adverse reactions and laboratory abnormalities with a difference between arms of ≥5%, respectively, compared to placebo in SPOTLIGHT.

Table 3. Adverse Reactions (≥15%) in Patients Treated with VYLOY in SPOTLIGHT with a Difference Between Arms of ≥5% Compared to Placebo
Adverse Reaction | VYLOY with mFOLFOX6 n=279 |  | Placebo with mFOLFOX6 n=278
Adverse Reaction | All Grades % | Grade 3 or 4 % | All Grades % | Grade 3 or 4 %
Gastrointestinal disorders
Nausea | 82 | 16 | 61 | 7
Vomiting | 67 | 16 | 36 | 6
Metabolism and nutrition disorders
Decreased appetite | 47 | 6 | 34 | 3.2
General disorders and administration site conditions
Peripheral edema | 18 | 0.7 | 9 | 0

Table 4. Laboratory Abnormalities (≥ 15%) in SPOTLIGHT with a Difference Between Arms of ≥ 5% Compared to Placebo
Laboratory Abnormality | VYLOY with mFOLFOX6 [The denominator used to calculate the rate varied from 271 to 272 based on the number of patients with a baseline value and at least one post-treatment value.] |  | Placebo with mFOLFOX6
Laboratory Abnormality | All Grades % | Grade 3 or 4 % | All Grades % | Grade 3 or 4 %
Albumin decreased | 78 | 4.4 | 47 | 1.1
Potassium decreased | 28 | 11 | 21 | 6
Glucose decreased | 45 | 0.4 | 35 | 0.4
Sodium decreased | 29 | 5 | 21 | 2.9

GLOW

The safety of VYLOY was evaluated in GLOW in patients with locally advanced unresectable or metastatic gastric/GEJ cancer who received at least one dose of VYLOY at an 800 mg/m^2 initial dose followed by 600 mg/m^2 subsequent doses every 3 weeks in combination with CAPOX [see Clinical Studies (14)]. The median duration of exposure to VYLOY in combination with CAPOX was 4.4 months (range: 0.03 to 30.7 months).

Serious adverse reactions occurred in 47% of patients treated with VYLOY in combination with CAPOX; the most common serious adverse reactions (≥2%) were vomiting (6%), nausea (4.3%), decreased appetite (3.9%), decreased platelet count (3.1%), upper gastrointestinal hemorrhage (2.8%), diarrhea (2.8%), pneumonia (2.4%), pulmonary embolism (2.3%), and pyrexia (2.0%). Fatal adverse reactions occurred in 8% of patients who received VYLOY in combination with CAPOX including sepsis (1.2%), pneumonia (0.4%), death (0.8%), upper gastrointestinal hemorrhage (0.8%), cerebral hemorrhage (0.8%), abdominal infection (0.4%), acute respiratory distress syndrome (0.4%), cardio‑respiratory arrest (0.4%), decreased platelet count (0.4%), disseminated intravascular coagulation (0.4%), dyspnea (0.4%), gastric perforation (0.4%), hemorrhagic ascites (0.4%), procedural complication (0.4%), sudden death (0.4%), and syncope (0.4%).

Permanent discontinuation of VYLOY due to an adverse reaction occurred in 19% of patients; the most common adverse reaction leading to discontinuation (≥2%) was vomiting.

Dosage interruption of VYLOY due to an adverse reaction occurred in 55% of patients; the most common adverse reactions leading to dose interruption (≥2%) were nausea, vomiting, neutropenia, thrombocytopenia, anemia, fatigue, infusion-related reaction, and abdominal pain.

Tables 5 and 6 summarize the most common (≥15%) adverse reactions and laboratory abnormalities with a difference between arms of ≥5%, respectively compared to placebo in GLOW.

Table 5. Adverse Reactions (≥15%) in Patients Treated with VYLOY in GLOW with a Difference Between Arms of ≥5% Compared to Placebo
Adverse Reaction | VYLOY; with CAPOX; n=254 |  | Placebo; with CAPOX; n=249
Adverse Reaction | All Grades; % | Grade 3 or 4; % | All Grades; % | Grade 3 or 4; %
Gastrointestinal disorders
Nausea | 69 | 9 | 50 | 2.4
Vomiting | 66 | 12 | 31 | 3.6
Metabolism and nutrition disorders
Decreased appetite | 41 | 7 | 34 | 1.6
Blood and lymphatic system disorders
Neutropenia | 20 | 7 | 14 | 2.8
Investigations
Weight decreased | 20 | 0.4 | 10 | 0.4

Other clinically relevant adverse reactions (<15%) in GLOW with a difference between arms of 5% compared to placebo included peripheral edema.

Table 6. Laboratory Abnormalities (≥15%) in Patients Treated with VYLOY in GLOW with a Difference Between Arms of ≥5% Compared to Placebo
Laboratory Abnormality | VYLOY with CAPOX [The denominator used to calculate the rate varied from 237 to 238 based on the number of patients with a baseline value and at least one post-treatment value.] |  | Placebo with CAPOX
Laboratory Abnormality | All Grades; % | Grade 3 or 4; % | All Grades; % | Grade 3 or 4; %
Albumin decreased | 66 | 3.8 | 47 | 1.7
Leukocytes decreased | 66 | 6 | 60 | 8
Neutrophils decreased | 76 | 21 | 70 | 14
Glucose decreased | 24 | 0 | 18 | 0

8 USE IN SPECIFIC POPULATIONS

8.1 Pregnancy

Risk Summary

There are no data with VYLOY use in pregnant women to inform any drug-associated risks. Embryo-fetal toxicity was not observed in pregnant mice intravenously administered zolbetuximab-clzb [see Data]. VYLOY should only be given to a pregnant woman if the benefit outweighs the potential risk.

The background risk of major birth defects and miscarriage for the indicated population is unknown. In the U.S. general population, the estimated background risk of major birth defects and miscarriage in clinically recognized pregnancies is 2%-4% and 15%-20%, respectively.

Data

Animal Data

In an embryo-fetal development toxicity study, zolbetuximab-clzb was intravenously administered to pregnant mice during the period of organogenesis and did not result in embryo-fetal toxicity at doses up to 300 mg/kg (approximately 1.9 times the recommended clinical dose based on AUC). Zolbetuximab-clzb crossed the placental barrier resulting in higher fetal serum concentrations on Day 18 of gestation than maternal serum concentrations on Day 16 of gestation.

8.2 Lactation

Risk Summary

There are no data on the presence of zolbetuximab-clzb in human milk, the effects on the breastfed child, or the effects on milk production. Because antibodies may be excreted in human milk and because of the potential for adverse reactions in a breastfed child, advise a lactating woman not to breastfeed during treatment with VYLOY and for 8 months after the last dose.

8.3 Females and Males of Reproductive Potential

VYLOY is used in combination with fluoropyrimidine- or platinum-containing chemotherapy. Refer to the Full Prescribing Information of fluoropyrimidine- and platinum-containing chemotherapy products for pregnancy testing, contraception, and infertility information.

8.4 Pediatric Use

The safety and effectiveness of VYLOY in pediatric patients have not been established.

8.5 Geriatric Use

Of the 533 patients in clinical studies of VYLOY in combination with mFOLFOX6 or CAPOX, 34% (n=179) were over 65 years, and 5% were over 75 years (n=28) [see Clinical Studies (14)]. No overall differences in safety or effectiveness were observed between patients aged 65 years or older and younger patients.

11 DESCRIPTION

Zolbetuximab-clzb is a chimeric (mouse/human) antibody composed of variable regions derived from mouse anti-human claudin-18 isoform 2 monoclonal antibody and constant regions derived from human IgG1. The molecular weight is approximately 147 kDa.

VYLOY (zolbetuximab-clzb) for injection is provided as a sterile, preservative-free, white to off-white lyophilized powder in single-dose vials for intravenous use. VYLOY is supplied as 100 mg or 300 mg per vial and requires reconstitution with Sterile Water for Injection, USP, (5 mL or 15 mL) resulting in a clear to slightly opalescent, colorless to slightly yellow solution with a final concentration of 20 mg/mL. Each mL of reconstituted solution contains 20 mg of zolbetuximab-clzb, arginine (23.24 mg), polysorbate 80 (0.21 mg), sucrose (51.30 mg), and phosphoric acid to adjust pH to 6.0.

12 CLINICAL PHARMACOLOGY

12.1 Mechanism of Action

Zolbetuximab-clzb is a claudin 18.2 (CLDN18.2)-directed cytolytic antibody that depletes CLDN18.2-positive cells via antibody-dependent cellular cytotoxicity (ADCC) and complement-dependent cytotoxicity (CDC). Zolbetuximab-clzb in combination with chemotherapy had increased antitumor activity in CLDN18.2-expressing mouse tumor models compared to zolbetuximab-clzb or chemotherapy alone.

12.2 Pharmacodynamics

The exposure-response relationships for efficacy and safety at the recommended dosages of zolbetuximab-clzb in patients with locally advanced unresectable or metastatic HER2-negative gastric or gastroesophageal junction adenocarcinoma whose tumors are CLDN18.2 positive have not been fully characterized.

12.3 Pharmacokinetics

Following a 2-hour intravenous infusion, zolbetuximab-clzb exhibited dose-proportional pharmacokinetics at doses ranging from 33 mg/m^2 to 1000 mg/m^2 (0.04 times to 1.25 times the recommended first dose). When administered at a first dose of 800 mg/m^2 followed by subsequent doses of 600 mg/m^2 every 3 weeks, steady state was achieved by 18 weeks with a geometric mean (coefficient of variation [CV]%) Cmax of 415 (22%) mcg/mL and AUCtau of 3149 (37%) day•mcg/mL.

Distribution

The estimated geometric mean (CV%) of the steady state volume of distribution of zolbetuximab-clzb was 14.0 (59%) L.

Metabolism

Zolbetuximab-clzb is expected to be catabolized into small peptides and amino acids.

Elimination

The estimated geometric mean (CV%) of the clearance (CL) and t1/2 of zolbetuximab-clzb was 0.013 (44%) L/h and 41 (62%) days, respectively.

Specific Populations

The following factors had no clinically important effect on the clearance of zolbetuximab-clzb: age (range: 22 to 83 years), sex, race including White (50%), Asian (42%), Black (0.8%), mild to moderate (CLcr ≥30 to <90 mL/min) renal impairment and mild hepatic impairment (total bilirubin (TB) ≤upper limit of normal (ULN) and AST >ULN, or TB >1 to 1.5 x ULN and any AST). The effect of severe renal impairment, and moderate to severe hepatic impairment is unknown.

12.6 Immunogenicity

The observed incidence of anti-drug antibody (ADA) is highly dependent on the sensitivity and specificity of the assay. Differences in assay methods preclude meaningful comparisons of the incidence of ADA in the studies described below with the incidence of ADA in other studies, including those of VYLOY or of other zolbetuximab products.

During the approximately 30-month period of treatment with VYLOY 800/600 mg/m^2 every 3 weeks in combination with mFOLFOX6 or CAPOX in the clinical studies SPOTLIGHT and GLOW, the incidence of anti-zolbetuximab-clzb antibody formation was 9.5% (46 of 485 ADA-evaluable patients).

Because of the low occurrence of ADAs, the effect of these antibodies on the pharmacokinetics, safety and/or effectiveness of VYLOY is unknown.

13 NONCLINICAL TOXICOLOGY

13.1 Carcinogenesis, Mutagenesis, Impairment of Fertility

No studies in animals have been performed with zolbetuximab-clzb to evaluate carcinogenicity, mutagenicity, or impairment of fertility.

14 CLINICAL STUDIES

SPOTLIGHT

The efficacy of VYLOY in combination with mFOLFOX6 was evaluated in SPOTLIGHT (NCT03504397), a double‑blind, randomized, multicenter study that enrolled 565 patients with locally advanced unresectable or metastatic HER2-negative gastric or GEJ adenocarcinoma whose tumors were CLDN18.2 positive. CLDN18.2 positivity (defined as ≥75% of tumor cells demonstrating moderate to strong membranous CLDN18 staining) was determined by immunohistochemistry on gastric or GEJ tumor tissue specimens from all patients with the VENTANA CLDN18 (43‑14A) RxDx Assay performed in a central laboratory. Patients were excluded from the study if they had a complete or partial gastric outlet syndrome, or history of central nervous system metastases.

Patients were randomized 1:1 to receive VYLOY in combination with mFOLFOX6 (n=283) or placebo in combination with mFOLFOX6 (n=282). VYLOY was administered intravenously at an initial dose of 800 mg/m^2 (Day 1 of cycle 1) followed by subsequent doses of 600 mg/m^2 every 3 weeks in combination with up to 12 treatments (4 cycles) of mFOLFOX6 (oxaliplatin 85 mg/m^2, folinic acid (leucovorin or local equivalent) 400 mg/m^2, fluorouracil 400 mg/m^2 given as a bolus and fluorouracil 2400 mg/m^2 given as a continuous infusion) administered on Days 1, 15 and 29 of a 42-day cycle. After 12 treatments, patients were allowed to continue treatment with VYLOY, 5-fluorouracil and folinic acid (leucovorin or local equivalent) at the discretion of the investigator, until progression of disease or unacceptable toxicity.

Treatment with VYLOY continued until RECIST v1.1-defined progression of disease as determined by an independent review committee (IRC) or a subsequent anticancer treatment was initiated. Tumor assessments were performed every 9 weeks up to and including Week 54, then every 12 weeks thereafter.

The major efficacy outcome measure was progression free survival (PFS) as assessed per RECIST v1.1 by IRC. Additional efficacy outcome measures were overall survival (OS), objective response rate (ORR) and duration of response (DOR) as assessed per RECIST v1.1 by IRC.

The study population characteristics were median age of 61 (range: 20-86); 62% were male; 48% were White, 34% Asian, 3.0% American Indian or Alaska, 1.2% Black or African American, 4.1% other racial groups, and race in 9% was unknown or missing; 78% non-Hispanic or Latino, 13% Hispanic or Latino, and ethnicity in 10% was missing; 98% had ECOG performance status (PS) of 0 or 1; 76% had gastric cancer, 24% had GEJ cancer; 84% were metastatic, 16% were locally advanced; and 29% had undergone prior gastrectomy. Subsequent anticancer therapy was received by 135 (48%) patients in the VYLOY in combination with mFOLFOX6 arm and 148 (53%) patients in the placebo in combination with mFOLFOX6 arm.

VYLOY in combination with mFOLFOX6 demonstrated a statistically significant improvement in PFS and OS compared with placebo in combination with mFOLFOX6.

Table 7, Figures 1 and 2 summarize the efficacy results for the SPOTLIGHT study.

Table 7. Efficacy Results in SPOTLIGHT
Endpoint | VYLOY with mFOLFOX6 n=283 | Placebo with mFOLFOX6 n=282
Progression Free Survival
Number (%) of patients with events | 146 (51.6) | 167 (59.2)
Median in months (95% CI) [Based on Kaplan-Meier estimate.] | 10.6 (8.9, 12.5) | 8.7 (8.2, 10.3)
Hazard ratio (95% CI) [Stratification factors were region, number of metastatic sites and prior gastrectomy from IRT.] , [Based on a stratified Cox proportional hazards model.] | 0.751 (0.598, 0.942)
1-sided p-value, [Based on a 1-sided stratified log-rank test.] | 0.0066
Overall survival
Number (%) of patients with events | 149 (52.7) | 177 (62.8)
Median in months (95% CI) | 18.2 (16.4, 22.9) | 15.5 (13.5, 16.5)
Hazard ratio (95% CI), | 0.750 (0.601, 0.936)
1-sided p-value, | 0.0053
Objective Response Rate (CR + PR) [Based on confirmed response.]
ORR (%) (95% CI) [Based on binomial distribution (Clopper-Pearson).] | 40.3 (34.5, 46.3) | 39.7 (34.0, 45.7)
Complete response rate (%) | 14 (4.9) | 8 (2.8)
Partial response rate (%) | 100 (35.3) | 104 (36.9)
Duration of Response | N=114 | N=112
Median in months (95% CI) | 10.3 (8.3, 10.9) | 10.5 (7.7, 13.3)

Figure 1. Kaplan Meier Plot of Progression Free Survival, SPOTLIGHT Study

Figure 2. Kaplan Meier Plot of Overall Survival, SPOTLIGHT Study

GLOW

The efficacy of VYLOY in combination with CAPOX was evaluated in GLOW (NCT03653507), a double-blind, randomized, multicenter study that enrolled 507 patients with locally advanced unresectable or metastatic HER2-negative gastric or GEJ adenocarcinoma whose tumors were CLDN18.2 positive. CLDN18.2 positivity (defined as ≥75% of tumor cells demonstrating moderate to strong membranous CLDN18 staining) was determined by immunohistochemistry on gastric or GEJ tumor tissue specimens from all patients with the VENTANA CLDN18 (43-14A) RxDx Assay performed in a central laboratory. Patients were excluded from the study if they had a complete or partial gastric outlet syndrome, or history of central nervous system metastases.

Patients were randomized 1:1 to receive VYLOY in combination with CAPOX (n=254) or placebo in combination with CAPOX (n=253). VYLOY was administered intravenously at an initial dose of 800 mg/m^2 (Day 1 of cycle 1) followed by a subsequent dose of 600 mg/m^2 every 3 weeks in combination with up to 8 treatments (8 cycles) of CAPOX administered on Day 1 (oxaliplatin 130 mg/m^2) and on Days 1 to 14 (capecitabine 1000 mg/m^2) of a 21-day cycle. After 8 treatments of oxaliplatin, patients were allowed to continue treatment of VYLOY and capecitabine at the discretion of the investigator, until progression of disease or unacceptable toxicity.

Treatment with VYLOY continued until RECIST v1.1-defined progression of disease as determined by IRC or subsequent anticancer treatment was initiated. Tumor assessments were performed every 9 weeks up to and including Week 54, then every 12 weeks thereafter.

The major efficacy outcome measure was PFS as assessed per RECIST v1.1 by IRC. Additional efficacy outcome measures were OS, ORR, and DOR as assessed per RECIST v1.1 by IRC.

The study population characteristics were median age of 60 years (range: 21-83); 62% were male; 62% were Asian, 36% were White and race in 1.4% was missing; 95% non-Hispanic or Latino, 3.4% were Hispanic or Latino and ethnicity in 1.4% was missing; 99% had ECOG performance status (PS) of 0 or 1; 84% had primary gastric cancer, 16% had primary gastroesophageal adenocarcinoma; 88% were metastatic, 12% were locally advanced; and 27% had undergone prior gastrectomy.

VYLOY in combination with CAPOX demonstrated a statistically significant improvement in PFS and OS compared with placebo in combination with CAPOX.

Table 8, Figures 3 and 4 summarize the efficacy results for the GLOW study.

Table 8. Efficacy Results in GLOW
Endpoint | VYLOY with CAPOX n=254 | Placebo with CAPOX n=253
Progression Free Survival
Number (%) of patients with events | 137 (53.9) | 172 (68.0)
Median in months (95% CI) [Based on Kaplan-Meier estimate.] | 8.2 (7.5, 8.8) | 6.8 (6.1, 8.1)
Hazard ratio (95% CI) [Stratification factors were region, number of metastatic sites and prior gastrectomy from IRT.] , [Based on a stratified Cox proportional hazards model.] | 0.687 (0.544, 0.866)
1-sided p-value, [Based on a 1-sided stratified log-rank test.] | 0.0007
Overall survival
Number (%) of patients with events | 144 (56.7) | 174 (68.8)
Median in months (95% CI) | 14.4 (12.3, 16.5) | 12.2 (10.3, 13.7)
Hazard ratio (95% CI), | 0.771 (0.615, 0.965)
1-sided p-value, | 0.0118
Objective Response Rate (CR + PR) [Based on confirmed response.]
ORR (%) (95% CI) [Based on binomial distribution (Clopper-Pearson).] | 32.3 (26.6, 38.4) | 31.2 (25.6, 37.3)
Complete response rate (%) | 6 (2.4) | 2 (0.8)
Partial response rate (%) | 76 (29.9) | 77 (30.4)
Duration of Response | N=82 | N=79
Median in months (95% CI) | 8.3 (6.3, 11.4) | 6.2 (6.0, 7.6)

Figure 3. Kaplan Meier Plot of Progression Free Survival, GLOW Study

Figure 4. Kaplan Meier Plot of Overall Survival, GLOW Study

16 HOW SUPPLIED/STORAGE AND HANDLING

VYLOY (zolbetuximab-clzb) for injection 100 mg and 300 mg are supplied as a sterile, preservative-free, white to off-white lyophilized powder in single-dose vials. VYLOY vials are available in the following packages:

- Carton of one 100 mg single-dose vial (NDC 0469-3425-10)
- Carton of one 300 mg single-dose vial (NDC 0469-4425-30)

Store VYLOY vials refrigerated at 2ºC to 8ºC (36ºF to 46ºF) in the original carton. Do not freeze. Do not shake.

17 PATIENT COUNSELING INFORMATION

Advise the patient to read the FDA-approved patient labeling (Patient Information).

Hypersensitivity reactions, including anaphylaxis and infusion-related reactions
Advise patients of the risk of hypersensitivity reactions including anaphylaxis and infusion-related reactions and to contact their healthcare provider right away if they experience symptoms of a hypersensitivity or infusion-related reaction during or after the administration of VYLOY. [see Warnings and Precautions (5.1)].

Severe nausea and vomiting
Advise patients of the risk of severe nausea and vomiting and to immediately contact their healthcare provider if they experience persistent or worsening nausea or vomiting [see Warnings and Precautions (5.2)].

Lactation
Advise women not to breastfeed during treatment with VYLOY and for 8 months after the last dose of VYLOY [see Use in Specific Populations (8.2)].

Manufactured by:
Astellas Pharma US, Inc.
Northbrook, Illinois 60062

U.S. License 2124

All trademarks are the property of their respective owners.

©2025 Astellas Pharma US, Inc.

00119-ZOL-USA

PATIENT INFORMATION

VYLOY® (vye-LOY)

(zolbetuximab-clzb)

for injection

What is VYLOY?

VYLOY is a prescription medicine used to treat adults with cancer of the stomach (gastric cancer) or cancer located where the esophagus joins the stomach (gastroesophageal junction cancer). VYLOY is used in combination with chemotherapy that contains fluoropyrimidine and platinum as the first treatment when your gastric or gastroesophageal junction cancer:

- cannot be removed with surgery or has spread to other parts of the body,
- is HER2-negative, and
- your tumor tests positive for “claudin (CLDN) 18.2.”

It is not known if VYLOY is safe and effective in children.

Before receiving VYLOY, tell your healthcare provider about all of your medical conditions, including if you:

- have nausea or vomiting.
- are pregnant or plan to become pregnant. It is not known if VYLOY will harm your unborn baby.
- are breastfeeding or plan to breastfeed. It is not known if VYLOY passes into your breast milk. Do not breastfeed during treatment with VYLOY and for 8 months after the last dose.

Tell your healthcare provider about all the medicines you take, including prescription and over-the-counter medicines, vitamins, and herbal supplements.

How will I receive VYLOY?

- VYLOY will be given to you by intravenous (IV) infusion into your vein.
- Your healthcare provider will decide how much VYLOY you will receive.
- You will usually receive VYLOY every 2 or 3 weeks based on the chemotherapy chosen by your healthcare provider.
- Your healthcare provider will decide how many treatments you need.

What are the possible side effects of VYLOY?

VYLOY may cause serious side effects, including:

- Allergic reactions, including anaphylaxis and infusion related reactions. Allergic reactions are common during treatment with VYLOY and can sometimes be serious. Serious allergic reactions can happen during or after your VYLOY infusion, including life-threatening allergic reactions and serious infusion-related reactions that may lead to death. Your healthcare provider will monitor you during your infusion and for 2 hours after or longer if needed. Tell your healthcare provider or get emergency medical help right away if you get any of the following symptoms of a serious allergic reaction during or after your infusion of VYLOY:

- itchy, raised bumps on the skin (hives)
- coughing that does not go away
- nausea or vomiting
- stomach (abdominal) pain
- increased saliva

- breathing problems such as wheezing
- throat tightness or change in voice
- fever
- chest discomfort
- chills or shaking
- back pain

- Severe nausea and vomiting. Nausea and vomiting are common during treatment with VYLOY and can sometimes be severe. Nausea and vomiting happened more often during the first treatment cycle. Before you receive each VYLOY infusion, your healthcare provider will give you medicines to help prevent nausea and vomiting. Tell your healthcare provider right away if nausea or vomiting does not go away or gets worse.

The most common side effects of VYLOY include:

- tiredness
- decreased appetite
- diarrhea
- tingling or numbness of the arms or legs
- stomach (abdominal) pain
- constipation
- decreased weight

- fever
- decreased white blood cells, red blood cells and platelets
- decreased protein (albumin) in the blood
- changes in kidney function tests
- changes in blood sugar (glucose)
- changes in liver function tests
- changes in body salts (electrolytes) in your blood

Your healthcare provider may slow the rate of your infusion, temporarily stop, or completely stop treatment with VYLOY if you have certain side effects.

These are not all of the possible side effects of VYLOY.

Call your doctor for medical advice about side effects. You may report side effects to FDA at 1-800-FDA-1088.

General information about the safe and effective use of VYLOY.

Medicines are sometimes prescribed for purposes other than those listed in a Patient Information leaflet. You can ask your pharmacist or healthcare provider for information about VYLOY that is written for health professionals.

What are the ingredients in VYLOY?

Active ingredient: zolbetuximab-clzb

Inactive ingredients: arginine, polysorbate 80, sucrose, and phosphoric acid to adjust pH.

Manufactured by:
Astellas Pharma US, Inc.
Northbrook, Illinois 60062

U.S. License 2124

©2025 Astellas Pharma US, Inc.

00119-ZOL-USA

For more information, go to www.VYLOY.com or call 1-888-727-7003.

This Patient Information has been approved by the U.S. Food and Drug Administration. Revised: 6/2025

PACKAGE/LABEL PRINCIPAL DISPLAY PANEL- 100 mg/vial

NDC 0469-3425-10
Rx Only

VYLOY®
zolbetuximab-clzb
FOR INJECTION

100 mg/vial

For intravenous infusion only
Must reconstitute and dilute before use

One Single-dose vial. Discard unused portion

PACKAGE/LABEL PRINCIPAL DISPLAY PANEL- 300 mg/vial

NDC 0469-4425-30
Rx Only

VYLOY®
zolbetuximab-clzb
FOR INJECTION

300 mg/vial

For intravenous infusion only
Must reconstitute and dilute before use

One Single-dose vial. Discard unused portion